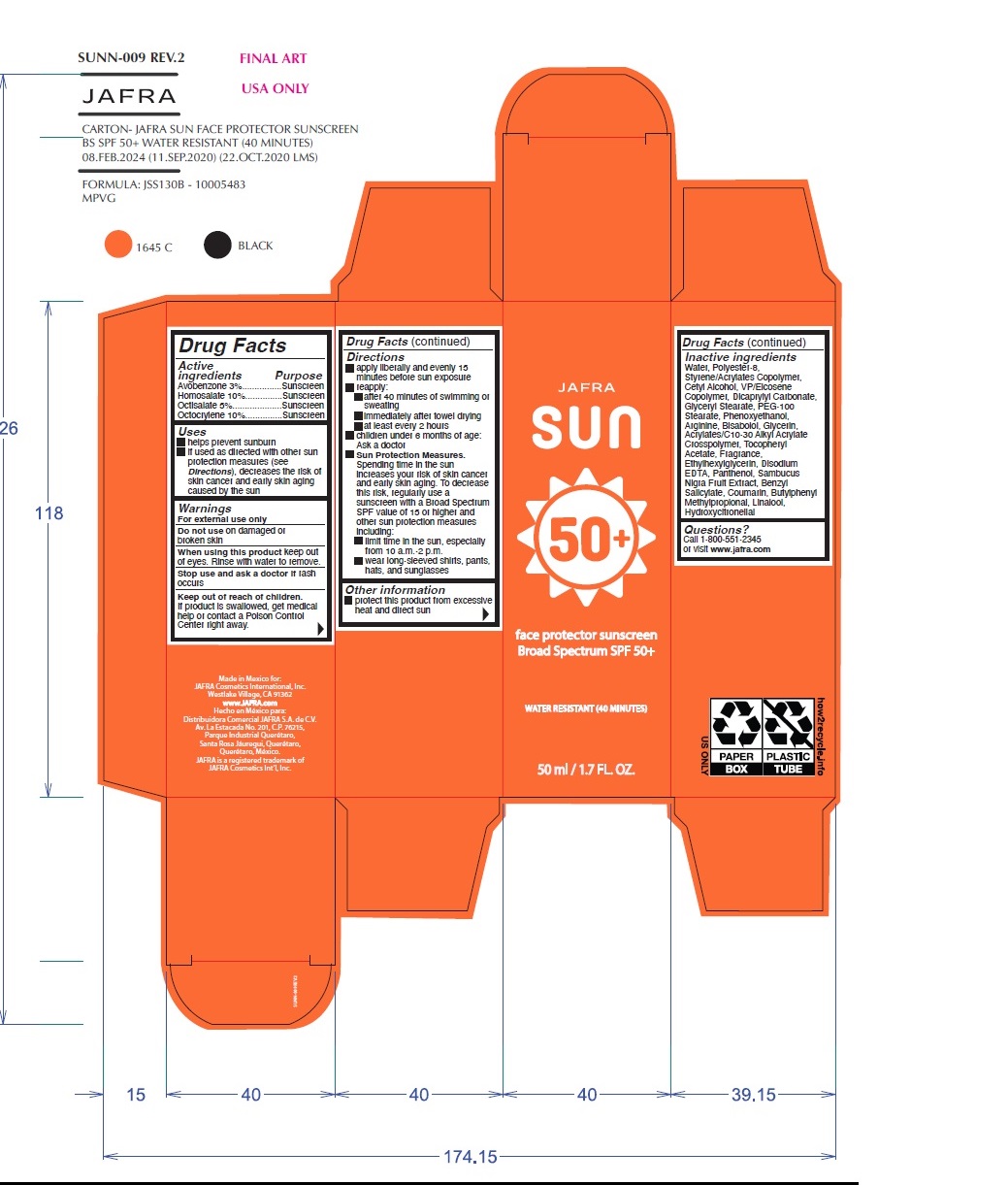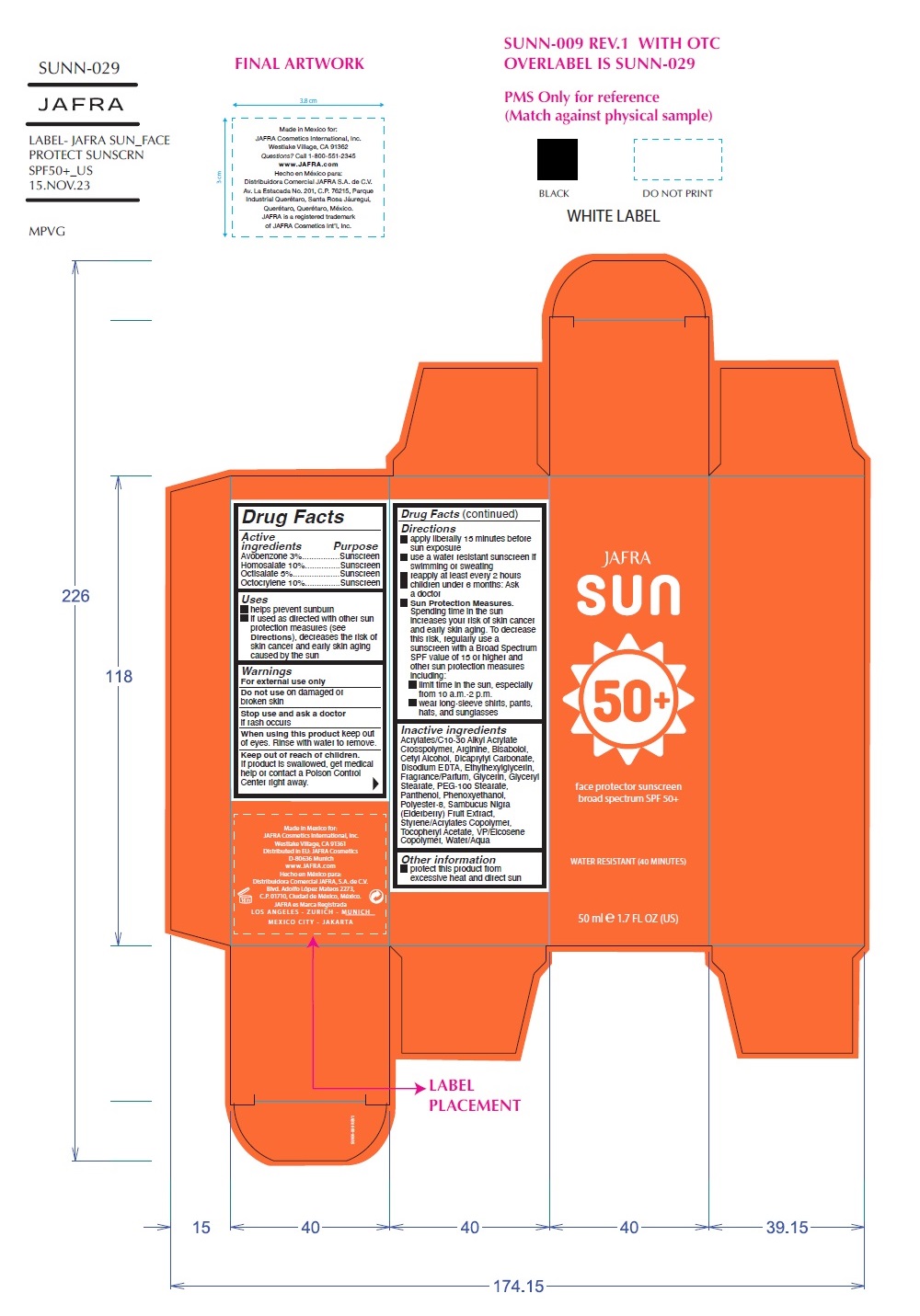 DRUG LABEL: Sun face protector sunscreen broad spectrum SPF 50
NDC: 68828-295 | Form: CREAM
Manufacturer: Distribuidora Comercial Jafra, S.A. de C.V.
Category: otc | Type: HUMAN OTC DRUG LABEL
Date: 20251021

ACTIVE INGREDIENTS: OCTISALATE 5 g/100 mL; OCTOCRYLENE 10 g/100 mL; AVOBENZONE 3 g/100 mL; HOMOSALATE 10 g/100 mL
INACTIVE INGREDIENTS: LEVOMENOL; CETYL ALCOHOL; DICAPRYLYL CARBONATE; ETHYLHEXYLGLYCERIN; PEG-100 STEARATE; PANTHENOL; .ALPHA.-TOCOPHEROL ACETATE; GLYCERYL MONOSTEARATE; POLYESTER-8 (1400 MW, CYANODIPHENYLPROPENOYL CAPPED); BENZYL SALICYLATE; ARGININE; GLYCERIN; EUROPEAN ELDERBERRY; VINYLPYRROLIDONE/EICOSENE COPOLYMER; WATER; PHENOXYETHANOL; EDETATE DISODIUM; CARBOMER COPOLYMER TYPE B (ALLYL PENTAERYTHRITOL CROSSLINKED); COUMARIN; BUTYLPHENYL METHYLPROPIONAL; LINALOOL, (+/-)-; HYDROXYCITRONELLAL

Jafra face protector sunscreen broad spectrum SPF 50+

Active Ingredients Purpose

Avobenzone 3%..............Sunscreen

Homosalate 10%.............Sunscreen

Octisalate 5%..................Sunscreen

Octocrylene 10%.............Sunscreen

Uses

- helps prevent sunburn
- if used as directed with other sun protection measures (see Directions) , decreases the risk of skin cancer and early skin aging caused by the sun.

Warnings

For external use only

Do not use on damaged or broken skin

When using this product keep out of eyes. Rinse with water to remove.

Stop use and ask a doctor if rash occurs

Keep out of reach of children.If product is swallowed, get medical help or contact a Poison Control Center right away.

Directions

- Apply liberally and evenly 15 minutes before sun exposure
- reapply:

• after 40 minutes of swimming or sweating

• immediately after towel drying

• at least every 2 hours

- children under 6 months of age: Ask a doctor
- Sun Protection Measures.Spending time in the sun increases your risk of skin cancer and early skin aging. To decrease this risk, regularly use a sunscreen with a Broad Spectrum SPF value of 15 or higher and other sun protection measures including:

• limit time in the sun, especially from 10 a.m. - 2 p.m.
• wear long-sleeved shirts, pants, hats, and sunglasses

Other information

protect this product form excessive heat and direct sun

Inactive Ingredients

Water, Polyester-8, Styrene/Acrylates Copolymer, Cetyl Alcohol, VP/Eicosene Copolymer, Dicaprylyl Carbonate, Glyceryl Stearate, PEG -100 Stearate, Phenoxyethanol, Arginine, Bisabolol, Glycerin, Acrylates/C10-30 Alkyl Acrylate Crosspolymer, Tocopheryl Acetate, Fragrance, Ethylhexylglycerin, Disodium EDTA, Panthenol, Sambucus Nigra Fruit Extract, Benzyl Salicylate, Coumarin, Butylphenyl Methylpropional, Linalool, Hydroxycitronellal

OTHER SAFETY INFORMATION

Questions?Call 1-800-551-2345 or visit www.jafra.com